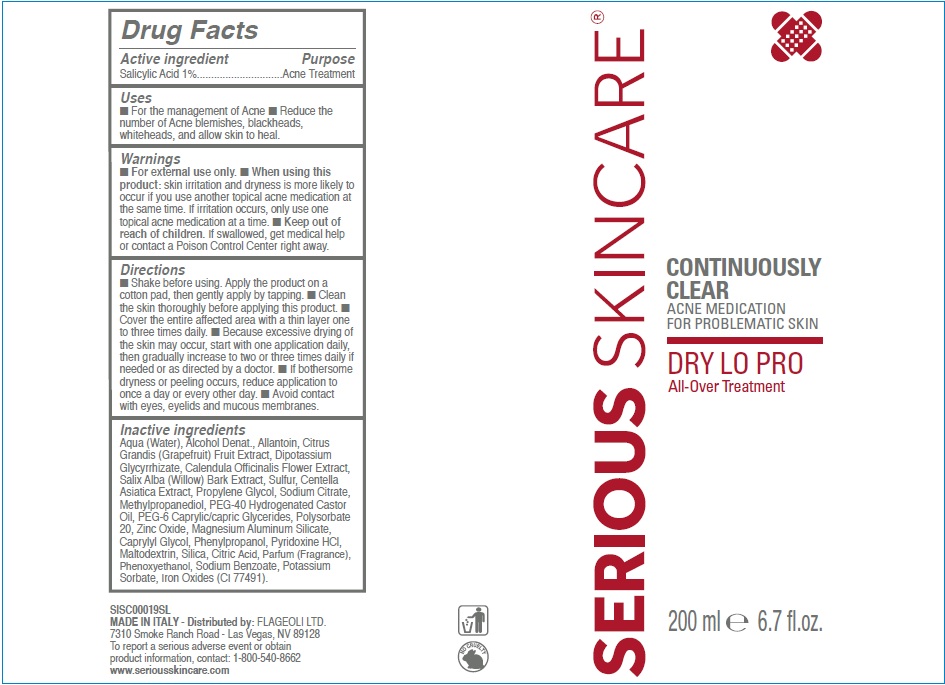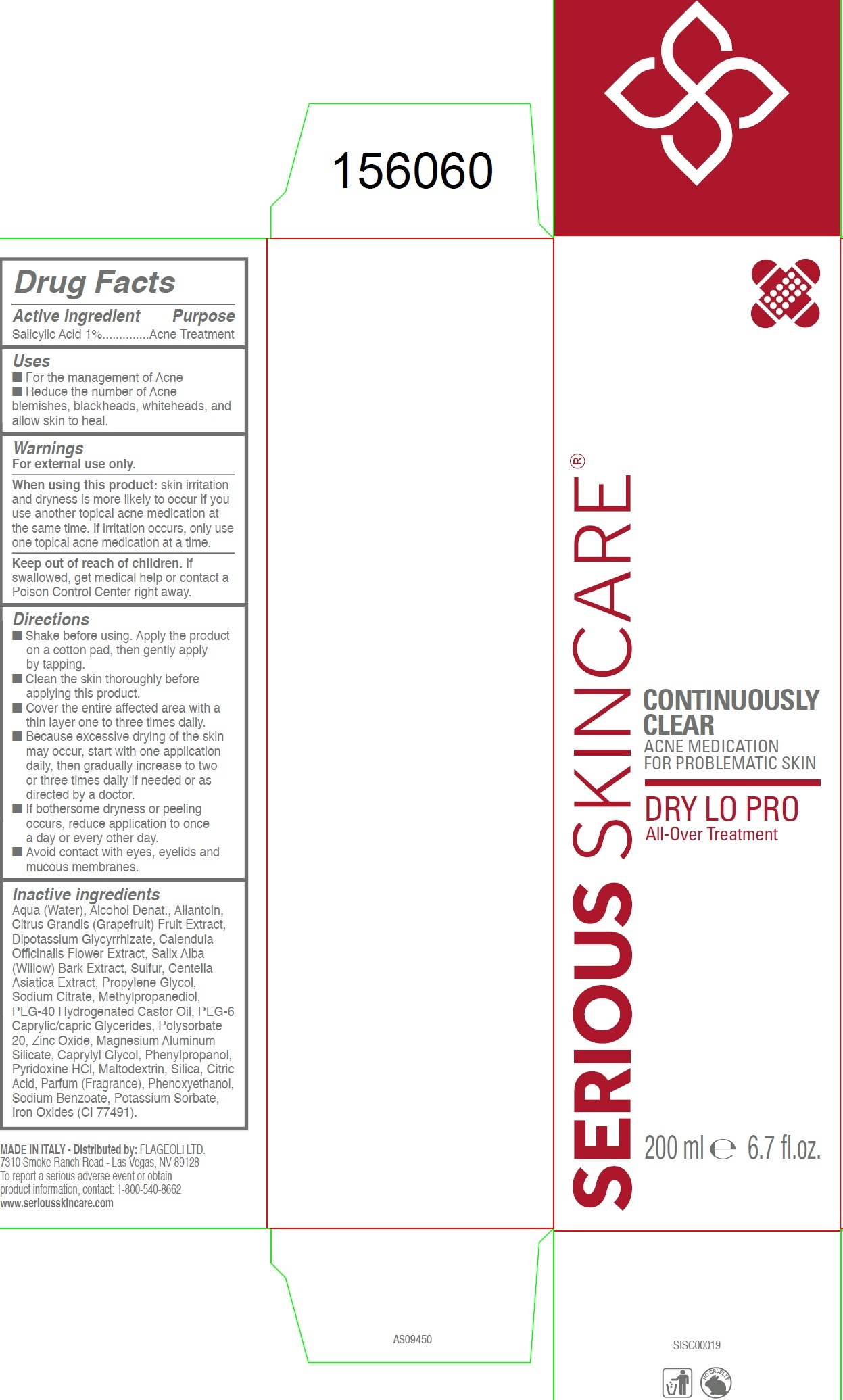 DRUG LABEL: Serious Skincare Continuously Clear Acne Medication For Problematic skin Dry Lo Pro All- Over Treatment
NDC: 53755-110 | Form: LOTION
Manufacturer: Flageoli Limited
Category: otc | Type: HUMAN OTC DRUG LABEL
Date: 20231212

ACTIVE INGREDIENTS: SALICYLIC ACID 10 mg/1 mL
INACTIVE INGREDIENTS: WATER; ALCOHOL; ALLANTOIN; PUMMELO; GLYCYRRHIZINATE DIPOTASSIUM; CALENDULA OFFICINALIS FLOWER; SALIX ALBA BARK; SULFUR; CENTELLA ASIATICA; PROPYLENE GLYCOL; SODIUM CITRATE; METHYLPROPANEDIOL; POLYOXYL 40 HYDROGENATED CASTOR OIL; PEG-6 CAPRYLIC/CAPRIC GLYCERIDES; POLYSORBATE 20; ZINC OXIDE; MAGNESIUM ALUMINUM SILICATE; CAPRYLYL GLYCOL; PHENYLPROPANOL; PYRIDOXINE HYDROCHLORIDE; MALTODEXTRIN; SILICON DIOXIDE; CITRIC ACID MONOHYDRATE; PHENOXYETHANOL; SODIUM BENZOATE; POTASSIUM SORBATE; FERRIC OXIDE RED

Serious Skincare Continuously Clear Acne Medication For Problematic skin Dry Lo Pro All- Over Treatment

Active ingredient

Salicylic Acid 1%

Purpose

Acne Treatment

Uses

- For the management of Acne
- Reduce the number of Acne blemishes, blackheads, whiteheads, and allow skin to heal.

Warnings

For external use only.

When using this product:

skin irritation and dryness is more likely to occur if you use another topical acne medication at the same time. If irritation occurs, only use one topical acne medication at a time.

Keep out of reach of children.

If swallowed, get medical help or contact a Poison Control Center right away.

Directions

- Shake before using. Apply the product on a cotton pad, then gently apply by tapping.
- Clean the skin thoroughly before applying this product.
- Cover the entire affected area with a thin layer one to three times daily.
- Because excessive drying of the skin may occur, start with one application daily, then gradually increase to two or three times daily if needed or as directed by a doctor.
- If bothersome dryness or peeling occurs, reduce application to once a day or every other day.
- Avoid contact with eyes, eyelids and mucous membranes.

Inactive ingredients

Aqua (Water), Alcohol Denat., Allantoin, Citrus Grandis (Grapefruit) Fruit Extract, Dipotassium Glycyrrhizate, Calendula Officinalis Flower Extract, Salix Alba (Willow) Bark Extract, Sulfur, Centella Asiatica Extract, Propylene Glycol, Sodium Citrate, Methylpropanediol, PEG-40 Hydrogenated Castor Oil, PEG-6 Caprylic/capric Glycerides, Polysorbate 20, Zinc Oxide, Magnesium Aluminum Silicate, Caprylyl Glycol, Phenylpropanol, Pyridoxine HCl, Maltodextrin, Silica, Citric Acid, Parfum (Fragrance), Phenoxyethanol, Sodium Benzoate, Potassium Sorbate, Iron Oxides (CI 77491).